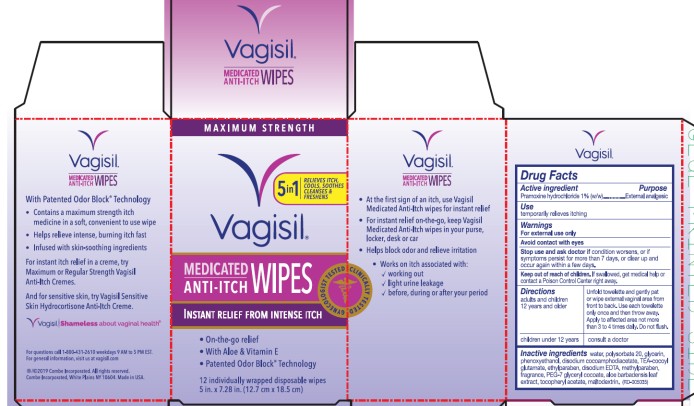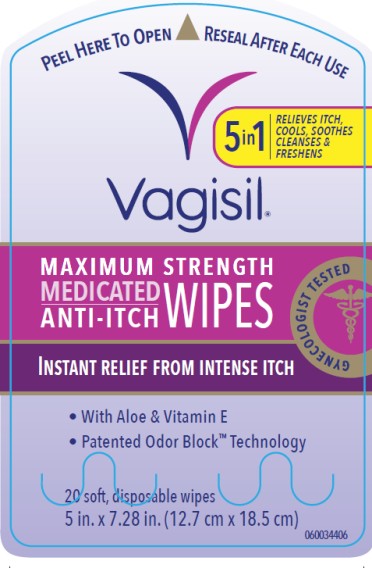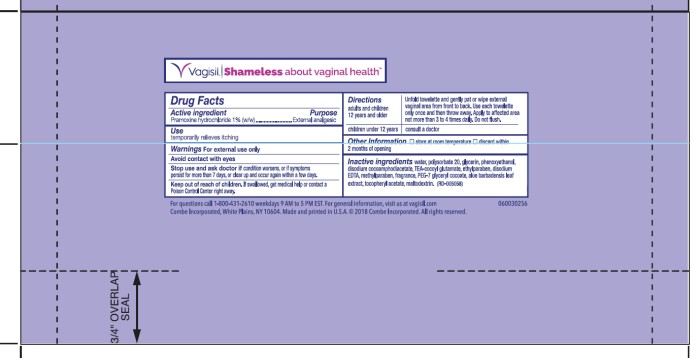 DRUG LABEL: VAGISIL Anti-Itch Medicated Wipes Maximum Strength
NDC: 11509-5035 | Form: CLOTH
Manufacturer: Combe Incorporated
Category: otc | Type: HUMAN OTC DRUG LABEL
Date: 20241212

ACTIVE INGREDIENTS: PRAMOXINE HYDROCHLORIDE 10 mg/1 g
INACTIVE INGREDIENTS: WATER; POLYSORBATE 20; GLYCERIN; PHENOXYETHANOL; DISODIUM COCOAMPHODIACETATE; TRIETHANOLAMINE COCOYL GLUTAMATE; ETHYLPARABEN; EDETATE DISODIUM; METHYLPARABEN; PEG-7 GLYCERYL COCOATE; ALOE VERA LEAF; .ALPHA.-TOCOPHEROL ACETATE, DL-; MALTODEXTRIN

Vagisil Medicated Anti-Itch Wipes Maximum Strength

VAGISIL Anti-Itch Medicated Wipes

Drug Facts

Active ingredient

Pramoxine hydrochloride 1% (w/w)

Purpose

External analgesic

Use

temporarily relieves itching

Warnings

For external use only

Avoid contact with eyes

Stop use and ask doctor if

condition worsens, or if symptoms persist for more than 7 days, or clear up and occur again within a few days

Keep out of reach of children.

If swallowed, get medical help or contact a Poison Control Center right away.

Directions

adults and children 12 years and older | Unfold towelette and gently pat or wipe external vaginal area from front to back. Use each towelette only once and then throw away. Apply to affected area not more than 3 to 4 times daily. Do not flush.
children under 12 years | consult a doctor

Inactive ingredients

water, polysorbate 20, glycerin, phenoxyethanol, disodium cocoamphodiacetate, TEA-cocoyl glutamate, ethylparaben, disodium EDTA, methylparaben, fragrance, PEG-7 glyceryl cocoate, aloe barbadensis leaf extract, tocopheryl acetate, maltodextrin

VAGISIL Maximum Strength Medicated Anti-Itch Wipes

Drug Facts

Active ingredient

Pramoxine hydrochloride 1% (w/w)

Purpose

External analgesic

Use

Temporarily relieves itching

Warnings

For external use only

Avoid contact with eyes

Stop use and ask doctor if

condition worsens, or if symptoms persist for more than 7 days, or clear up and occur again within a few days

Keep out of reach of children.

If swallowed, get medical help or contact a Poison Control Center right away.

Directions

adults and children 12 years and older | Unfold towelette and gently pat or wipe external vaginal area from front to back. Use each towelette only once and then throw away. Apply to affected area not more than 3 to 4 times daily. Do not flush.
children under 12 years | consult a doctor

Other information

store at room temperature

discard within 2 months of opening

Inactive ingredients

water, polysorbate 20, glycerin, phenoxyethanol, disodium cocoamphodiacetate, TEA-cocoyl glutamate, ethylparaben, disodium EDTA, methylparaben, fragrance, PEG-7 glyceryl cocoate, aloe barbadensis leaf extract, tocopheryl acetate, maltodextrin

Principal Display Panel

Maximum Strength
Vagisil®

Medicated Anti-Itch Wipes

Instant Relief From Intense Itch

Gynecologist Tested

Clinically Tested

- On-the-go relief
- With Aloe & Vitamin E
- Patented Odor Block Technology

12 individually wrapped disposable wipes

5 in. x 7.28 in. (12.7 cm x 18.5 cm)

Principal Display Panel

Vagisil®
Maximum Strength

Medicated Anti-Itch Wipes

Gynecologist Tested

Instant Relief From Intense Itch

- With Aloe & Vitamin E
- Patented Odor Block Technology

20 soft, disposable wipes

5 in. x 7.28 in. (12.7 cm x 18.5 cm)